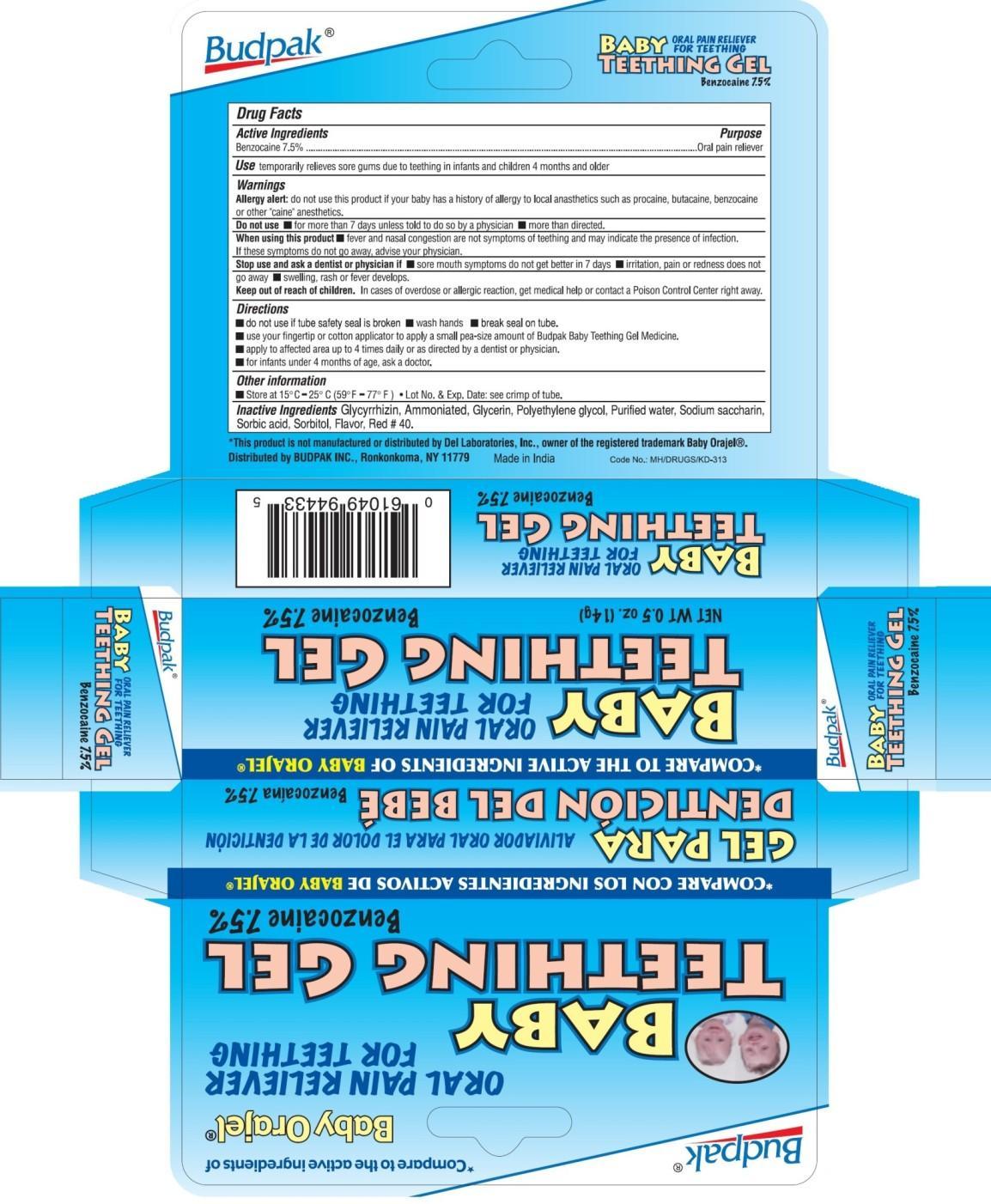 DRUG LABEL: Budpak Baby Teething Oral Pain Reliever
NDC: 27293-015 | Form: GEL
Manufacturer: Budpak Inc.
Category: otc | Type: HUMAN OTC DRUG LABEL
Date: 20131226

ACTIVE INGREDIENTS: BENZOCAINE 7.5 g/100 g
INACTIVE INGREDIENTS: GLYCYRRHIZIN, AMMONIATED; GLYCERIN; POLYETHYLENE GLYCOLS; WATER; SACCHARIN SODIUM; SORBIC ACID; SORBITOL; FD&C RED NO. 40

Budpak Baby Teething Oral Pain Reliever Gel

Active Ingredient

Benzocaine 7.5%

Purpose

Oral pain reliever

Use

temporarily relieves sore gums due to teething in infants and children 4 months and older

Warnings

Allergy alert: do not use this product if your baby has a history of allergy to local anesthetics such as procaine, butacaine, benzocaine or other "caine" anesthetics.

Do not use

- for more than 7 days unless told to do so by a physician
- more than directed

When using this product

- fever and nasal congestion are not symptoms of teething and may indicate the presence of infection. If these symptoms do not go away, advise your physician.

STOP USE

Stop using and ask a dentist or physician if

- sore mouth symptoms do not get better in 7 days
- irritation, pain or redness does not go away
- swelling, rash or fever develops

Keep out of reach of children.

In cases of overdose or allergic reaction, get medical help or contact a Poison Control Center right away

Directions

- do not use if tube safety seal is broken
- wash hands
- break seal on tube
- use your fingertip or cotton applicator to apply a small pea-size amount of Budpak Baby Teething Gel Medicine.
- apply to affected area up to 4 times daily or as directed by a dentist or physician.
- for infants under 4 months of age, ask a doctor

Other information

- Store at 15°C to 25 °C (59°F to 77°F)
- Lot No. & Exp. Date: see crimp of tube

Inactive Ingredients

Glycyrrhizin Ammoniated, Glycerin, Polyethylene glycol, Purified water, Sodium saccharin, Sorbic acid, Sorbitol, Flavor, Red #40.

PRINCIPAL DISPLAY PANEL

BUDPAK BABY TEETHING PAIN RELIEVER GEL

Benzocaine 7.5%

NET WT 0.5 OZ. (14 g)